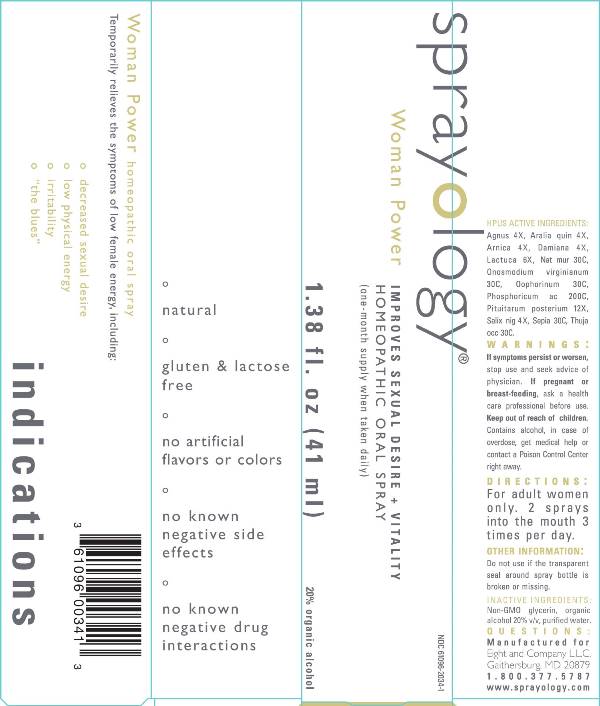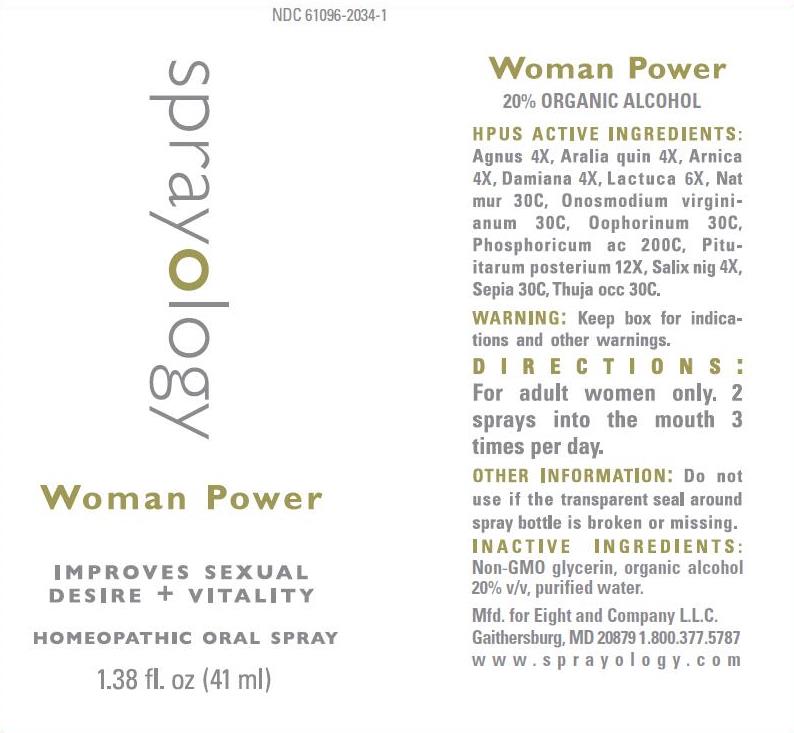 DRUG LABEL: Woman Power
NDC: 61096-2034 | Form: LIQUID
Manufacturer: Eight and Company L.L.C
Category: homeopathic | Type: HUMAN OTC DRUG LABEL
Date: 20251217

ACTIVE INGREDIENTS: CHASTE TREE 4 [hp_X]/41 mL; AMERICAN GINSENG 4 [hp_X]/41 mL; ARNICA MONTANA 4 [hp_X]/41 mL; TURNERA DIFFUSA LEAFY TWIG 4 [hp_X]/41 mL; LACTUCA VIROSA 6 [hp_X]/41 mL; SODIUM CHLORIDE 30 [hp_C]/41 mL; ONOSMODIUM VIRGINIANUM WHOLE 30 [hp_C]/41 mL; SUS SCROFA OVARY 30 [hp_C]/41 mL; PHOSPHORIC ACID 200 [hp_C]/41 mL; SUS SCROFA PITUITARY GLAND 12 [hp_X]/41 mL; SALIX NIGRA BARK 4 [hp_X]/41 mL; SEPIA OFFICINALIS JUICE 30 [hp_C]/41 mL; THUJA OCCIDENTALIS LEAFY TWIG 30 [hp_C]/41 mL
INACTIVE INGREDIENTS: GLYCERIN; ALCOHOL; WATER

Woman Power

ACTIVE INGREDIENTS:

Agnus 4X, Aralia quin 4X, Arnica 4X, Damiana 4X, Lactuca 6X, Nat mur 30C, Onosmodium virginianum 30C, Oophorinum 30C, Phosphoricum ac 200C, Pituitarum posterium 12X, Salix nig 4X, Sepia 30C, Thuja occ 30C.

PURPOSE:

Temporarily relieves the symptoms of low female energy, including:

° decreased sexual desire
° low physical energy
° irritability
° "the blues"

WARNINGS:

If symptoms persist or worsen, stop use and seek advice of physician. If pregnant or breast-feeding, ask a health care professional before use. Keep out of reach of children. Contains alcohol, in case of overdose, get medical help or contact a Poison Control Center right away.

Keep out of reach of children. Contains alcohol, in case of overdose, get medical help or contact a Poison Control Center right away.

DIRECTIONS:

For adult women only. 2 sprays into the mouth 3 times per day.

OTHER INFORMATION:

Do not use if the transparent seal around spray bottle is broken or missing.

INDICATIONS:

Temporarily relieves the symptoms of low female energy, including:

º decreased sexual desire

º low physical energy

º irritability

º "the blues"

° natural

° gluten & lactose free

° no artificial flavors or colors

° no known negative side effects

° no known negative drug interactions

INACTIVE INGREDIENTS:

Non-GMO Glycerin, organic alcohol 20% v/v, purified water.

QUESTIONS:

Mfd. for Eight and Company L.L.C.

Gaithersburg, MD 20879 1.800.377.5787

www.sprayology.com

PACKAGE LABEL DISPLAY:

NDC 61096-2034-1

sprayology

Woman Power

IMPROVES SEXUAL

DESIRE + VITALITY

HOMEOPATHIC ORAL SPRAY

1.38 fl.oz (41 ml)